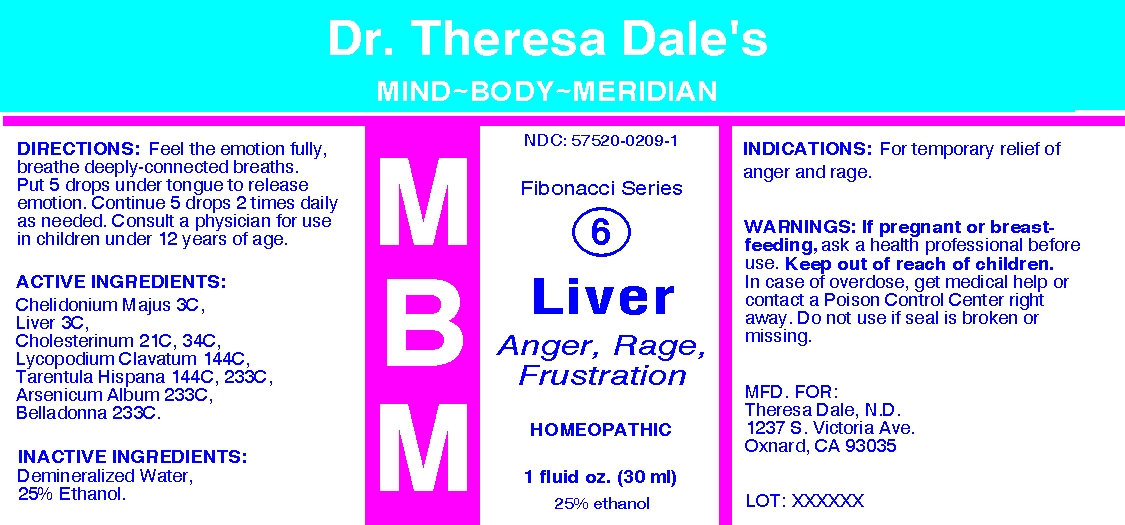 DRUG LABEL: MBM 6 Liver
NDC: 57520-0209 | Form: LIQUID
Manufacturer: Apotheca Company
Category: homeopathic | Type: HUMAN OTC DRUG LABEL
Date: 20100629

ACTIVE INGREDIENTS: CHELIDONIUM MAJUS 3 [hp_C]/1 mL; PORK LIVER 3 [hp_C]/1 mL; CHOLESTEROL 34 [hp_C]/1 mL; LYCOPODIUM CLAVATUM SPORE 144 [hp_C]/1 mL; LYCOSA TARANTULA 233 [hp_C]/1 mL; ARSENIC TRIOXIDE 233 [hp_C]/1 mL; ATROPA BELLADONNA 233 [hp_C]/1 mL
INACTIVE INGREDIENTS: WATER; ALCOHOL

MBM 6 Liver

ACTIVE INGREDIENT

ACTIVE INGREDIENTS: Chelidonium majus 3C, Liver 3C, Cholesterinum 21C, 34C, Lycopodium clavatum 144C, Tarentula hispana 144C, 233C, Arsenicum album 233C, Belladona 233C.

PURPOSE

INDICATIONS: For temporary relief of anger and rage.

WARNINGS

WARNINGS: If pregnant or breast-feeding, ask a health professional before use.

Keep out of reach of children. In case of overdose, get medical help or contact a Poison Control Center right away.

Do not use if seal is broken or missing.

DOSAGE AND ADMINISTRATION

DIRECTIONS: Feel the emotion fully, breathe deeply-connected breaths. Put 5 drops under tongue to release emotion. Continue 5 drops 2 times daily as needed. Consult a physician for use in children under 12 years of age.

INACTIVE INGREDIENTS: Demineralized water, 25% Ethanol

QUESTIONS

MFD. FOR:

Theresa Dale, N.D.

1237 S Victoria Ave.

Oxnard, CA 93035

PACKAGE LABEL

Dr. Theresa Dale's

MIND-BODY-MERIDIAN

Fibonacci Series

6

Liver

ANGER, RAGE, FRUSTRATION

HOMEOPATHIC

1 fluid oz. (30 ml)